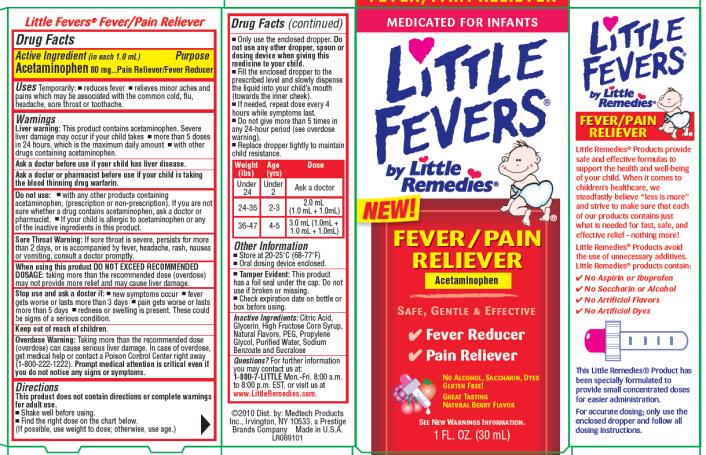 DRUG LABEL: Little Fevers by Little Remedies
NDC: 63029-601 | Form: LIQUID
Manufacturer: Medtech Products Inc.
Category: otc | Type: HUMAN OTC DRUG LABEL
Date: 20100702

ACTIVE INGREDIENTS: ACETAMINOPHEN .8 mL/1 mL
INACTIVE INGREDIENTS: HIGH FRUCTOSE CORN SYRUP; SODIUM BENZOATE; GLYCERIN; POLYETHYLENE GLYCOL; PROPYLENE GLYCOL; SUCRALOSE; WATER; ANHYDROUS CITRIC ACID

Little Fevers Little Remedies

Drug Facts

Active Ingredient

(in each 1.0 mL)

Acetaminophen 80mg

Purpose

Pain Reliever/Fever Reducer

Uses

Temporarily:

- reduces fever
- relieves minor aches and pains which may be associated with the common cold, flu, headache, sore throat or toothache.

Warnings

Liver warning: This product contains acetaminophen. Severe liver damage may occur if your child takes

- more than 5 doses in 24 hours, which is the maximum daily amount
- with other drugs containing acetaminophen.

Ask a doctor before use

if your child has liver disease.

Ask a doctor or pharmacist before use

if your child is taking the blood thinning drug warfarin.

Do not use:

- with any other products containing acetaminophen, (prescription or non-prescription). If you are not sure whether a drug contains acetaminophen, ask a doctor or pharmacist.
- If your child is allergic to acetaminophen or any of the inactive ingredients in this product.

Sore Throat Warning: If sore throat is severe, persists for more than 2 days, or is accompanied by fever, headache, rash, nausea or vomiting, consult a doctor promptly.

When using this product

DO NOT EXCEED RECOMMENDED DOSAGE: taking more than the recommended dose (overdose) may not provide more relief and may cause liver damage.

Stop use and ask a doctor if:

- new symptoms occur
- fever gets worse or lasts more than 3 days
- pain gets worse or lasts more than 5 days
- redness or swelling is present. These could be signs of a serious condition.

Overdose

Warning: Taking more than the recommended dose (overdose) can cause serious liver damage. In case of overdose, get medical help or contact a Poison Control Center right away

(1-800-222-1222). Prompt medical attention is critical even if you do not notice any signs or symptoms.

Directions

- This product does not contain directions or complete warnings for adult use.
- Shake well before using.
- Find the right dose on the chart below. (If possible, use weight to dose; otherwise, use age.)
- Only use the enclosed dropper. Do not use any other dropper, spoon or dosing device when giving this medicine to your child.
- Fill the enclosed dropper to the prescribed level and slowly dispense the liquid into your child’s mouth (towards the inner cheek).
- If needed, repeat dose every 4 hours while symptoms last.
- Do not give more than 5 times in any 24-hour period (see overdose warning).
- Replace dropper tightly to maintain child resistance.

Weight (Ibs) | Age (yrs) | Dose
Under 24 | Under 2 | Ask a doctor
24-35 | 2-3 | 2.0 mL (1.0 mL + 1.0mL)
36-47 | 4-5 | 3.0 mL (1.0mL + 1.0 mL + 1.0mL)

Other Information

- Store at 20-25°C (68-77°F)
- Oral dosing device enclosed.

- Tamper Evident: This product has a foil seal under the cap. Do not use if broken or missing.
- Check expiration date on bottle or box before using.

Inactive Ingredients:

Citric Acid, Glycerin, High Fructose Corn Syrup, Natural Flavors, PEG, Propylene Glycol, Purified Water, Sodium Benzoate and Sucralose

Questions?

For further information you may contact us at:

1-800-7-LITTLE Mon.-Fri. 8:00 a.m. to 8:00 p.m. EST, or visit us at www.LittleRemedies.com.

©2010 Dist. by: Medtech Products Inc., Irvington, NY 10533, a Prestige Brands Company Made in U.S.A.

LR089101

PRINCIPAL DISPLAY PANEL

MEDICATED FOR INFANTS
Little Fevers ®
by Little Remedies®
NEW!
FEVER/PAIN
RELIEVER
Acetaminophen
SAFE, GENTLE & EFFECTIVE
NATURAL BERRY FLAVOR
SEE NEW WARNINGS INFORMATION.
1 FL. OZ. (30 mL)